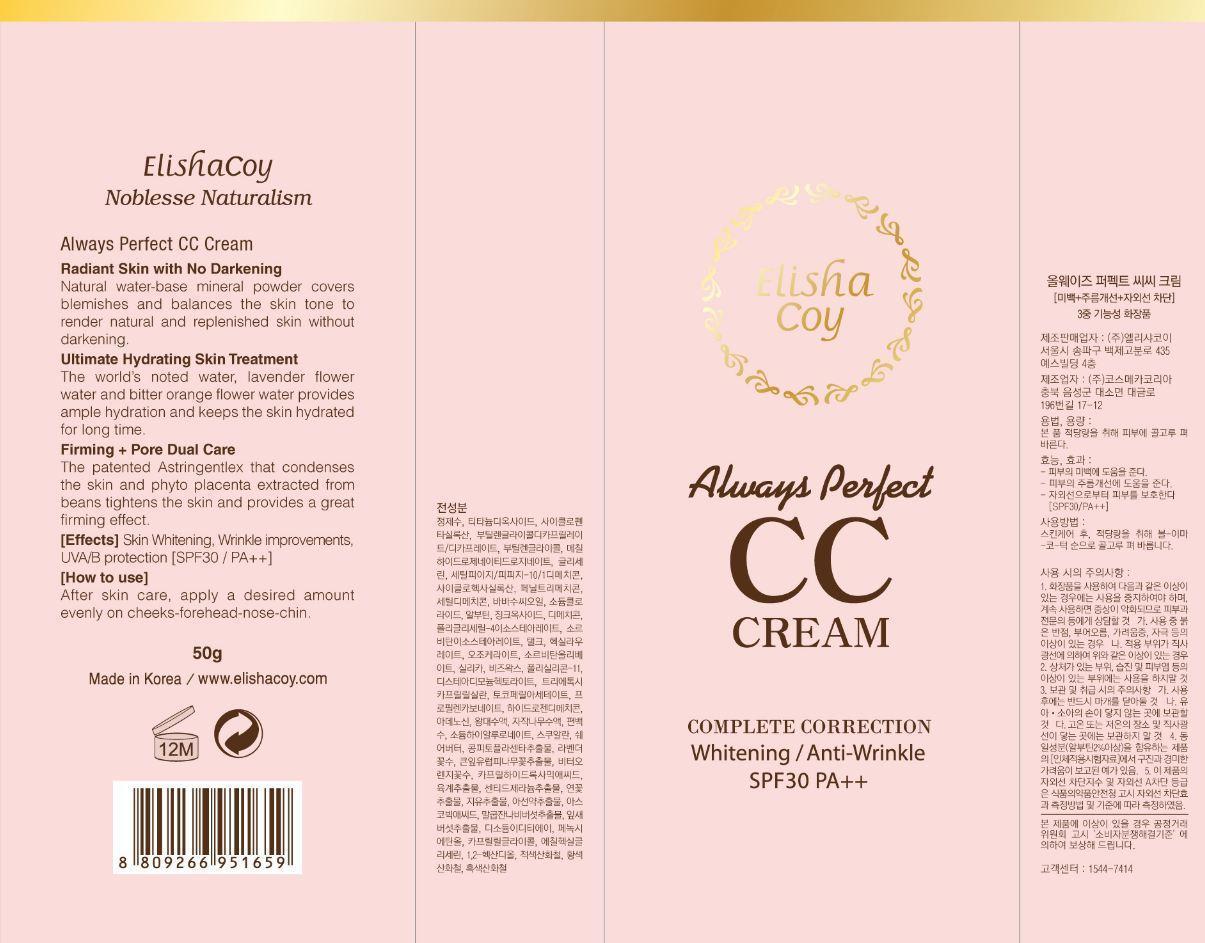 DRUG LABEL: Always Perfect CC
NDC: 53727-105 | Form: CREAM
Manufacturer: Cosmecca Korea Co., Ltd.
Category: otc | Type: HUMAN OTC DRUG LABEL
Date: 20140815

ACTIVE INGREDIENTS: TITANIUM DIOXIDE 5 g/50 g; ZINC OXIDE 3 g/50 g
INACTIVE INGREDIENTS: WATER; CYCLOMETHICONE 5; BUTYLENE GLYCOL DICAPRYLATE/DICAPRATE; BUTYLENE GLYCOL; METHYL HYDROGENATED ROSINATE; GLYCERIN; CETYL PEG/PPG-10/1 DIMETHICONE (HLB 2); CYCLOMETHICONE 6; PHENYL TRIMETHICONE; CETYL DIMETHICONE 150; SODIUM CHLORIDE; BABASSU SEED; ARBUTIN; DIMETHICONE; POLYGLYCERYL-4 ISOSTEARATE; SORBITAN ISOSTEARATE; TALC; HEXYL LAURATE; SILICON DIOXIDE; CERESIN; YELLOW WAX; DISTEARDIMONIUM HECTORITE; CAPRYLYL GLYCOL; PHENOXYETHANOL; ETHYLHEXYLGLYCERIN; TRIETHOXYCAPRYLYLSILANE; PROPYLENE CARBONATE; .ALPHA.-TOCOPHEROL ACETATE; SORBITAN OLIVATE; HYDROGEN; 1,2-HEXANEDIOL; ADENOSINE; EDETATE DISODIUM; SQUALANE; ASCORBIC ACID; SHEA BUTTER; TILIA PLATYPHYLLOS FLOWER; LAVANDULA ANGUSTIFOLIA FLOWER; CITRUS AURANTIUM FLOWER; LARICIFOMES OFFICINALIS WHOLE; PHYLLOSTACHYS RETICULATA RESIN; CHAMAECYPARIS OBTUSA WHOLE; BETULA PLATYPHYLLA VAR. JAPONICA RESIN; HYALURONATE SODIUM; UNCARIA GAMBIR WHOLE; SANGUISORBA OFFICINALIS ROOT; PELARGONIUM GRAVEOLENS WHOLE; NELUMBO NUCIFERA FLOWER; CINNAMON BARK OIL; ALCOHOL; SOYBEAN; GRIFOLA FRONDOSA WHOLE; CITRIC ACID MONOHYDRATE; SODIUM BENZOATE; POTASSIUM SORBATE; CAPRYLHYDROXAMIC ACID; FERRIC OXIDE RED

ACTIVE INGREDIENT

Titanium Dioxide (9.92%), Zinc Oxide (6.31%)

PURPOSE

Always Perfect CC Cream

Complete Correction

Whitening/Anti-Wrinkle

SPF30 PA++

Keep out of reach of children

INDICATIONS AND USAGE

ElishaCoy

Noblesse Naturalism

Always Perfect CC Cream

Radiant Skin with No Darkening

Natural water-base mineral powder covers blemishes and balances the skin tone to render natural and replenished skin without darkening.

Ultimate Hydrating Skin Treatment

The world's noted water, lavender flower water and bitter orange flower water provides ample hydration and keeps the skin hydrated for long time.

Firming + Pore Dual Care

The patented Astringentlex that condenses the skin and phyto placenta extracted from beans tightens the skin and provides a great firming effect.

[Effects] Skin Whitening, Wrinkle improvements, UVA/B protection [SPF30 PA++]

Warnings

DOSAGE AND ADMINISTRATION

[How to Use]

After skin care, apply a desired amount evenly on cheeks-forehead-nose-chin.

INACTIVE INGREDIENT

Water, Cyclopentasiloxane, Butylene Glycol Dicaprylate/Dicaprate, Butylene Glycol, Methyl Hydrogenated Rosinate, Glycerin, Cetyl PEG/PPG-10/1 Dimethicone, Cyclohexasiloxane, Phenyl Trimethicone, Cetyl Dimethicone, Sodium Chloride, Babassu (Orbignya Oleifera) Seed Oil, Arbutin, Dimethicone, Polyglyceryl-4 Isostearate, Sorbitan Isostearate, Talc, Hexyl Laurate, Silica, Ozokerite, Beeswax, Disteardimonium Hectorite, Caprylyl Glycol, Phenoxyethanol, Ethylhexylglycerin, Triethoxycaprylylsilane, Propylene Carbonate, Polysilicone-11, Tocopheryl Acetate, Sorbitan Olivate, Hydrogen Dimethicone, 1,2-Hexanediol, Adenosine, Disodium EDTA, Squalane, Ascorbic Acid, Shea Butter, Tilia Platyphyllos Flower Extract, Lavender Flower Water, Bitter Orange (Citrus Aurantium amara) Flower Water, Mushroom (Fomes Officinalis) Extract, Bamboo (Phyllostachis Bambusoides) Juice, Japanese Cypress (Chamaecyparis Obtusa) Water, Japanese White Birch (Betula Platyphylla Japonica) Juice, Sodium Hyaluronate, Catechu (Uncaria Gambir) Extract, Great Burnet (Sanguisorba Officinalis) Root Extract, Geranium (Pelargonium Graveolens) Extract, Lotus (Nelumbo Nucifera) Flower Extract, Cinnamon (Cinnamomum Zeylanicum) Bark Extract, Alcohol, Soybean (Glycine Soja Phytoplacenta) Extract, Grifola Frondosa Extract, Citric Acid, Sodium Benzoate, Potassium sorbate, Caprylhydroxamic Acid, Iron Oxides (CI 77492, CI 77491, CI 77499)